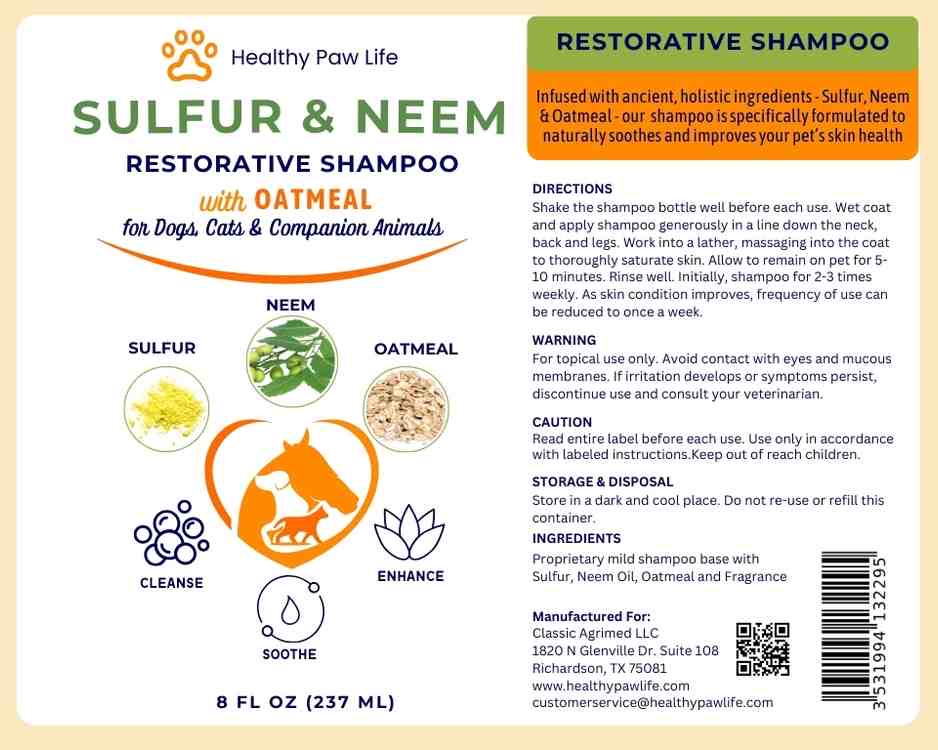 DRUG LABEL: HEALTHY PAW LIFE SULFUR NEEM
NDC: 86130-906 | Form: SHAMPOO
Manufacturer: CLASSIC AGRIMED LLC
Category: animal | Type: OTC ANIMAL DRUG LABEL
Date: 20250109

ACTIVE INGREDIENTS: SULFUR 9.5 g/237 g; AZADIRACHTA INDICA SEED OIL 1.2 g/237 g; OATMEAL 2.4 g/237 g

HEALTHY PAW LIFE SULFUR NEEM SHAMPOO

Infused with ancient, holistic ingredients - Sulfur, Neem & Oatmeal - our shampoo is specifically formulated to naturally soothes and improves your pet’s skin health

DIRECTIONS:

Shake the shampoo bottle well before each use. Wet coat and apply shampoo generously in a line down the neck, back and legs. Work into a lather, massaging into the coat to thoroughly saturate skin. Allow to remain on pet for 5-10 minutes. Rinse well. Initially, shampoo for 2-3 times weekly. As skin condition improves, frequency of use can be reduced to once a week.

WARNING:

For topical use only. Avoid contact with eyes and mucous membranes. If irritation develops or symptoms persist, discontinue use and consult your veterinarian.

CAUTION:

Read entire label before each use. Use only in accordance with labeled instructions.Keep out of reach children.

STORAGE & DISPOSAL:

Store in a dark and cool place. Do not re-use or refill this container.

INGREDIENTS:

Proprietary mild shampoo base with Sulfur, Neem Oil, Oatmeal and Fragrance

Manufactured For:

Classic Agrimed LLC